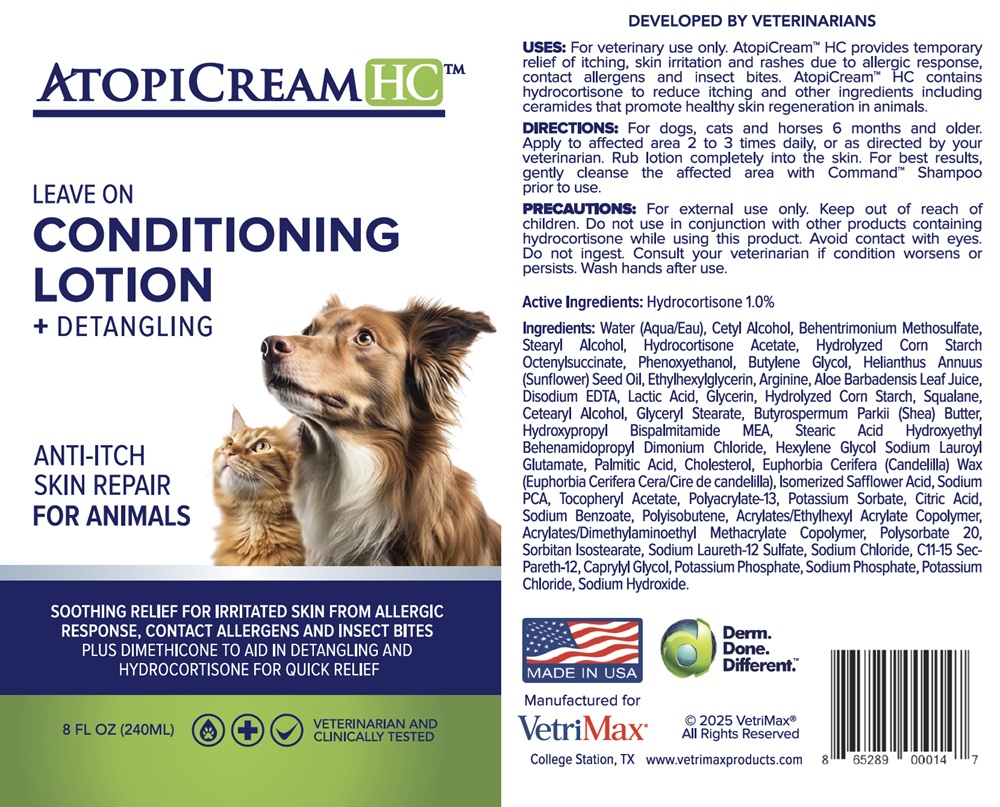 DRUG LABEL: AtopiCream HC
NDC: 86030-095 | Form: LOTION
Manufacturer: VetriMax Veterinary Products, LLC
Category: animal | Type: OTC ANIMAL DRUG LABEL
Date: 20251015

ACTIVE INGREDIENTS: HYDROCORTISONE 10 mg/1 mL
INACTIVE INGREDIENTS: WATER; CETYL ALCOHOL; BEHENTRIMONIUM METHOSULFATE; STEARYL ALCOHOL; HYDROCORTISONE ACETATE; STARCH, CORN; OCTENYLSUCCINIC ACID; PHENOXYETHANOL; BUTYLENE GLYCOL; HELIANTHUS ANNUUS (SUNFLOWER) SEED OIL; ETHYLHEXYLGLYCERIN; ARGININE; ALOE BARBADENSIS LEAF JUICE; EDETATE DISODIUM; LACTIC ACID; GLYCERIN; Squalane; Cetearyl Alcohol; Glyceryl Stearate; BUTYROSPERMUM PARKII (SHEA) BUTTER; HYDROXYPROPYL BISPALMITAMIDE MEA; STEARIC ACID; HYDROXYETHYL BEHENAMIDOPROPYL DIMONIUM CHLORIDE; HEXYLENE GLYCOL; SODIUM LAUROYL GLUTAMATE; PALMITIC ACID; CHOLESTEROL; EUPHORBIA CERIFERA (CANDELILLA) WAX; ISOMERIZED SAFFLOWER ACID; SODIUM PYRROLIDONE CARBOXYLATE; .ALPHA.-TOCOPHEROL ACETATE; POLYACRYLATE-13; POTASSIUM SORBATE; CITRIC ACID; SODIUM BENZOATE; POLYISOBUTYLENE (1300 MW); ACRYLATE/BUTYL ACRYLATE/ETHYLHEXYL ACRYLATE/METHYL METHACRYLATE COPOLYMER (6:1:2:1); POLYSORBATE 20; Sorbitan Isostearate; Sodium Laureth-12 Sulfate; Sodium Chloride; C11-15 SEC-PARETH-12; Caprylyl Glycol; Potassium Phosphate; Sodium Phosphate; POTASSIUM CHLORIDE; SODIUM HYDROXIDE

AtopiCream HC Therapeutic Skin Repair for Animals with Hydrocortisone

Uses:

For veterinary use only. AtopiCream™ HC provides temporary relief of
itching, skin irritation and rashes due to allergic response, contact allergens
and insect bites. AtopiCream™ HC contains hydrocortisone to reduce itching and
other ingredients including ceramides that promote healthy skin regeneration in
animals.

Directions:

For dogs, cats and horses 6 months and older. Apply to affected area 2 to 3 times daily, or as directed by your veterinarian. Rub lotion completely into skin. For best results, gently cleanse the affected area with Command™ Shampoo prior to use.

Precautions:

For external use only. Keep out of reach of children. Do not use in conjunction with other products containing hydrocortisone while using this product. Avoid contact with eyes. Do not ingest. Consult your veterinarian if condition worsens or persists. Wash hands after use.

Active Ingredients:

Hydrocortisone 1.0%

Ingredients:

Water (Aqua/Eau), Cetyl Alcohol, Behentrimonium Methosulfate, Stearyl Alcohol, Hydrocortisone Acetate, Hydrolyzed Corn Starch Octenylsuccinate, Phenoxyethanol, Butylene Glycol, Helianthus Annuus (Sunflower) Seed Oil, Ethylhexylglycerin, Arginine, Aloe Barbadensis Leaf Juice, Disodium EDTA, Lactic Acid, Glycerin, Hydrolyzed Corn Starch, Squalane, Cetearyl Alcohol, Glyceryl Stearate, Butyrospermum Parkii (Shea) Butter, Hydroxypropyl Bispalmitamide MEA, Stearic Acid Hydroxyethyl Behenamidopropyl Dimonium Chloride, Hexylene Glycol Sodium Lauroyl Glutamate, Palmitic Acid, Cholesterol, Euphorbia Cerifera (Candelilla) Wax (Euphorbia Cerifera Cera/Cire de candelilla), Isomerized Safflower Acid, Sodium PCA, Tocopheryl Acetate, Polyacrylate-13, Potassium Sorbate, Citric Acid, Sodium Benzoate, Polyisobutene, Acrylates/Ethylhexyl Acrylate Copolymer, Acrylates/Dimethylaminoethyl Methacrylate Copolymer, Polysorbate 20, Sorbitan Isostearate, Sodium Laureth-12 Sulfate, Sodium Chloride, Cll-15 Sec-Pareth-12, Caprylyl Glycol, Potassium Phosphate, Sodium Phosphate, Potassium Chloride, Sodium Hydroxide.